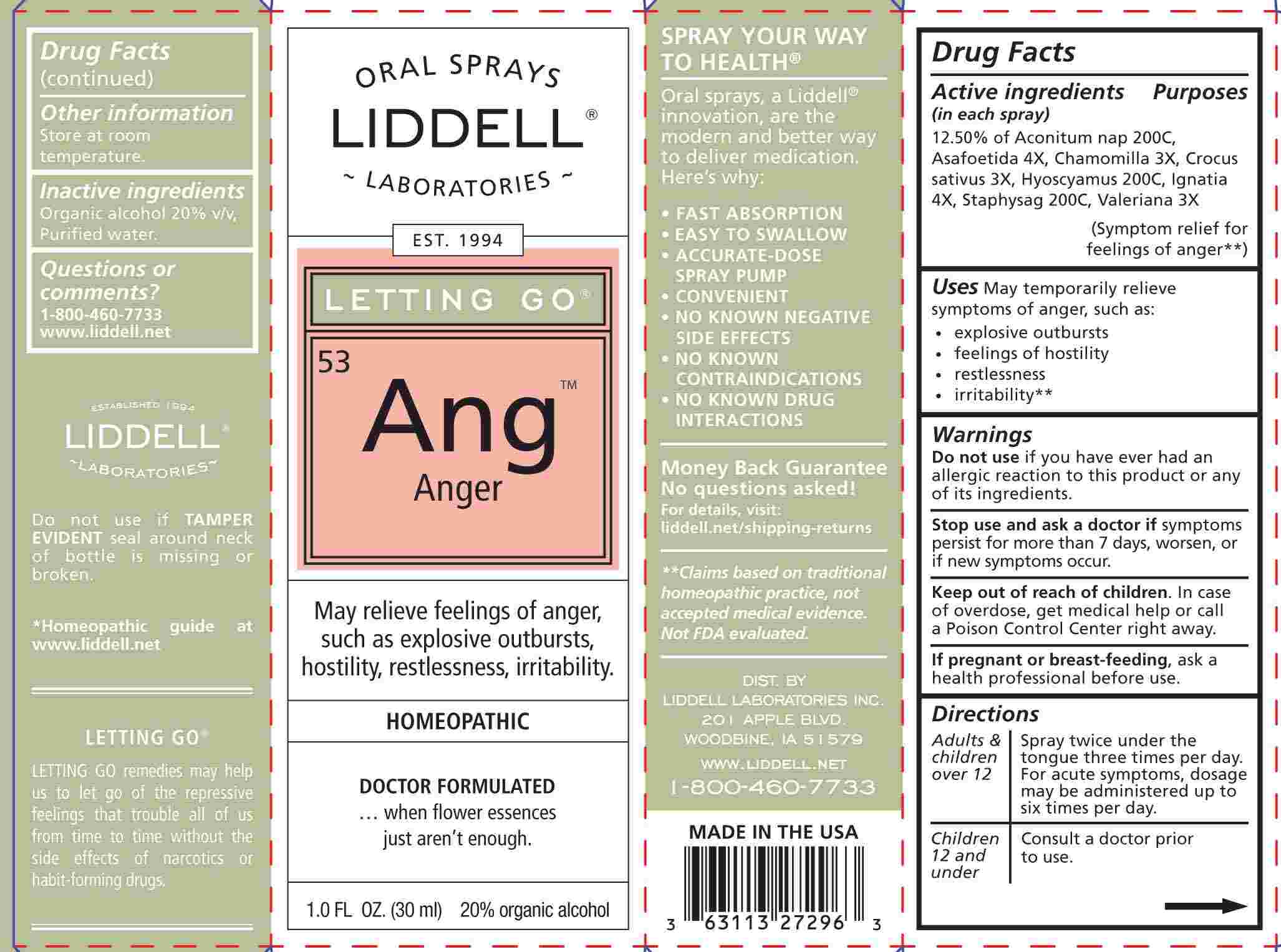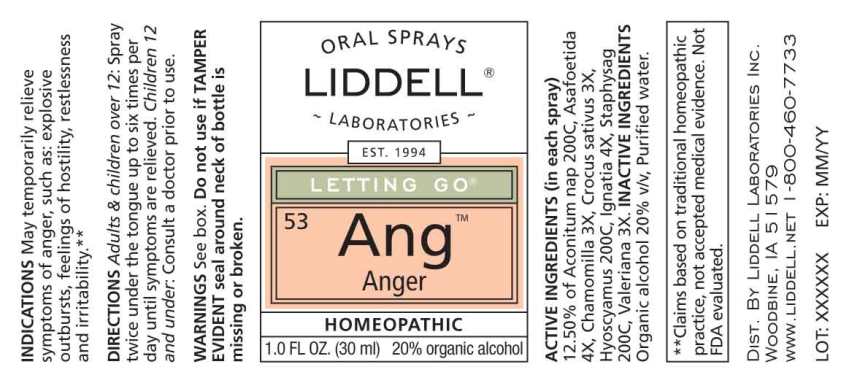 DRUG LABEL: Anger
NDC: 50845-0269 | Form: SPRAY
Manufacturer: Liddell Laboratories
Category: homeopathic | Type: HUMAN OTC DRUG LABEL
Date: 20231201

ACTIVE INGREDIENTS: ACONITUM NAPELLUS WHOLE 200 [hp_C]/1 mL; FERULA ASSA-FOETIDA RESIN 4 [hp_X]/1 mL; MATRICARIA CHAMOMILLA WHOLE 3 [hp_X]/1 mL; SAFFRON 3 [hp_X]/1 mL; HYOSCYAMUS NIGER 200 [hp_C]/1 mL; STRYCHNOS IGNATII SEED 4 [hp_X]/1 mL; DELPHINIUM STAPHISAGRIA SEED 200 [hp_C]/1 mL; VALERIAN 3 [hp_X]/1 mL
INACTIVE INGREDIENTS: water; ALCOHOL

DRUG FACTS:

ACTIVE INGREDIENTS:

(in each spray): 12.50% Aconitum napellus 200C, Asafoetida 4X, Chamomilla 3X, Crocus sativus 3X, Hyoscyamus niger 200C, Ignatia amara 4X, Staphysagria 200C, Valeriana officinalis 3X.

USES:

May temporarily relieve symptoms of anger, such as:

- explosive outbursts
- feelings of hostility
- restlessness
- irritability**

**Claims based on traditional homeopathic practice, not accepted medical evidence. Not FDA evaluated.

WARNINGS:

Do not use if you have ever had an allergic reaction to this product or any of its ingredients.

Stop use and ask a doctor if symptoms persist for more than 7 days, worsen, or if new symptoms occur.

Keep out of reach of children. In case of overdose, get medical help or call a Poison Control Center right away.

If pregnant or breast-feeding, ask a health professional before use.

Do not use if TAMPER EVIDENT seal around neck of bottle is missing or broken.

Store at room temperature.

DIRECTIONS:

Adults and children over 12: Spray twice under the tongue up to six times per day until symptoms are relieved.

Children 12 and under: Contact a doctor prior to use.

INACTIVE INGREDIENTS:

Organic alcohol 20% v/v, Purified water.

KEEP OUT OF REACH OF CHILDREN:

In case of overdose, get medical help or call a Poison Control Center right away.

USES:

May temporarily relieve symptoms of anger, such as:

- explosive outbursts
- feelings of hostility
- restlessness
- irritability**

**Claims based on traditional homeopathic practice, not accepted medical evidence. Not FDA evaluated.

QUESTIONS:

DIST. BY

LIDDELL LABORATORIES INC.

201 APPLE BLVD.

WOODBINE, IA 51579

WWW.LIDDELL.NET

1-800-460-7733

PACKAGE LABEL DISPLAY:

ORAL SPRAYS

LIDDELL
LABORATORIES

EST 1994

LETTING GO
53ANG

ANGER

May relieve feelings of anger,
such as explosive outbursts,
hostility, restlessness, irritability.

HOMEOPATHIC

DOCTOR FORMULATED

...when flower essences
just aren't enough.

1.0 FL. OZ. (30 ml)